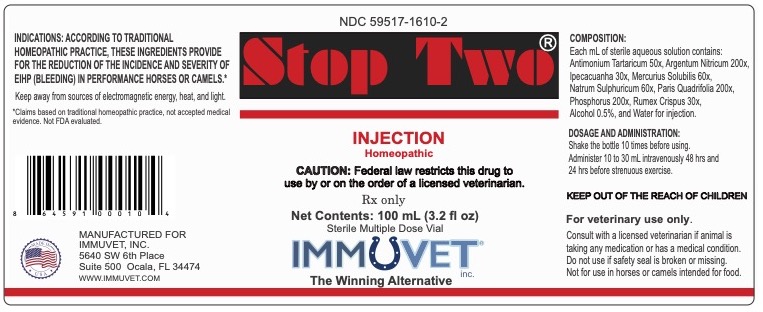 DRUG LABEL: Stop Two
NDC: 59517-1610 | Form: INJECTION
Manufacturer: Immuvet
Category: homeopathic | Type: PRESCRIPTION ANIMAL DRUG LABEL
Date: 20251104

ACTIVE INGREDIENTS: ANTIMONY POTASSIUM TARTRATE 50 [hp_X]/1.0 mL; SILVER NITRATE 200 [hp_X]/1.0 mL; IPECAC 30 [hp_X]/1.0 mL; MERCURIUS SOLUBILIS 60 [hp_X]/1.0 mL; SODIUM SULFATE 60 [hp_X]/1.0 mL; PARIS QUADRIFOLIA 200 [hp_X]/1.0 mL; PHOSPHORUS 15 [hp_X]/1.0 mL; RUMEX CRISPUS ROOT 30 [hp_X]/1.0 mL
INACTIVE INGREDIENTS: ALCOHOL; WATER

Stop Two

DESCRIPTION

Ingredient name Potency

Antimon Tartaricum 50x

Argentum Nitricum 200x

Ipecacuanha 30x

Mercurius Solubilis 60x

Natrum Sulph 60x

Paris Quadrifolia 200x

Phosphorus 15x, 200x

Rumex Crispus 30x

INDICATIONS AND USAGE

Prevention of equine Exercise-Induced Pulmonary Hemorrhage (EIPH)

- Stop Two® Injection Solution is a homeopathic drug product indicated for the prevention of Exercise-Induced Pulmonary Hemorrhage (EIPH) in horses and camels.

DOSAGE AND ADMINISTRATION

General Considerations

- Stop Two® Injection solution is to be administered i.v.

• Only licensed veterinarians with sufficient expertise in injecting drugs should administer the product.

Standard Dosage - for the prevention of equine Exercise-Induced Pulmonary Hemorrhage (EIPH):

10cc administered 48 hours before strenuous activity

20cc administered 24 hours before strenuous activity

Shake 10 times prior to use

CONTRAINDICATIONS

- There are no known contraindications for Stop Two® Injection solution.

WARNINGS AND PRECAUTIONS

None

ADVERSERE REACTIONS

Post-marketing Experience

• There have been no adverse reactions reported to date.

To report SUSPECTED ADVERSE REACTIONS, contact Immuvet at (352) 291-0200 or info@immuvet.com

OVERDOSAGE

No negative effects of an overdose have been reported and none are expected due to the homeopathic dilutions.

CLINICAL PHARMACOLOGY

Mechanism of Action

The exact mechanism of Stop Two® Injection solution is not fully understood.

Pharmacodynamics

Not applicable for homeopathic medicinal products.

Package Label - Principal Display Panel

Stop Two Injection™
Sterile Injectable Solution
100 mL Sterile Multiple Dose Vial
To reduce the incidence and severity of EIPH (bleeding) in performance horses and camels.
Caution: Federal law restricts this drug to use by or on the order of a licensed veterinarian.
Net contents:
100 mL